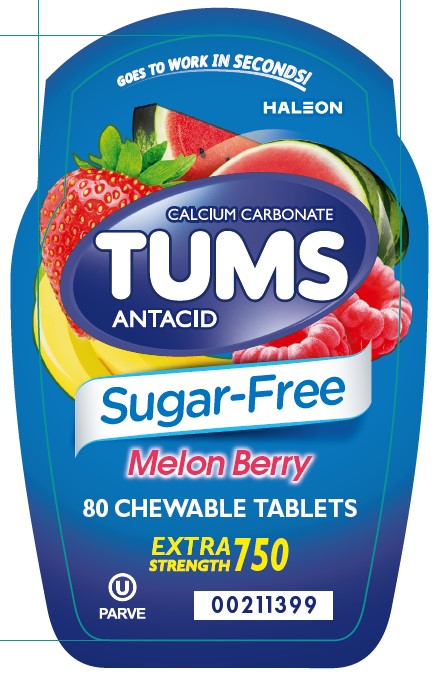 DRUG LABEL: TUMS
NDC: 0135-0155 | Form: TABLET, CHEWABLE
Manufacturer: Haleon US Holdings LLC
Category: otc | Type: HUMAN OTC DRUG LABEL
Date: 20241219

ACTIVE INGREDIENTS: CALCIUM CARBONATE 750 mg/1 1
INACTIVE INGREDIENTS: ACACIA; CALCIUM STEARATE; FD&C RED NO. 40; FD&C YELLOW NO. 5 ALUMINUM LAKE; ALUMINUM OXIDE; SORBITOL; SUCRALOSE

Drug Facts

Active ingredient (per tablet)

Calcium carbonate 750 mg

Purpose

Antacid

Uses

relieves

- heartburn
- acid indigestion
- sour stomach
- upset stomach associated with these symptoms

Warnings

Ask a doctor or pharmacist before use if you are

presently taking a prescription drug. Antacids may interact with certain prescription drugs.

When using this product

- do not take more than 10 tablets in 24 hours
- if pregnant do not take more than 6 tablets in 24 hours
- do not use the maximum dosage for more than 2 weeks, except under the advice and supervision of a doctor

Directions

- adults and children 12 years of age and over: chew 2 – 4 tablets as symptoms occur, or as directed by a doctor. Chew or crush tablets completely before swallowing.
- do not take for symptoms that persist for more than 2 weeks unless advised by a doctor

Other information

- each chewable tablet contains: elemental calcium 300 mg
- do not store above 25°C (77°F)
- contains FD&C Yellow No. 5 (tartrazine) as a color additive

Inactive ingredients

acacia gum, calcium stearate, FD&C red #40 alum lake, FD&C yellow #5 alum lake (tartrazine), flavors, sorbitol, sucralose

Questions or comments?

1-800-897-7535

Additional Information

Safety sealed – Do not use if printed inner seal beneath cap is missing or broken.

Gluten-Free

Principal Display Panel

GOES TO WORK IN SECONDS!

CALCIUM CARBONATE

TUMS

ANTACID

SUGAR-FREE

Melon Berry

80 CHEWABLE TABLETS

EXTRA STRENGTH 750

(U) PARVE